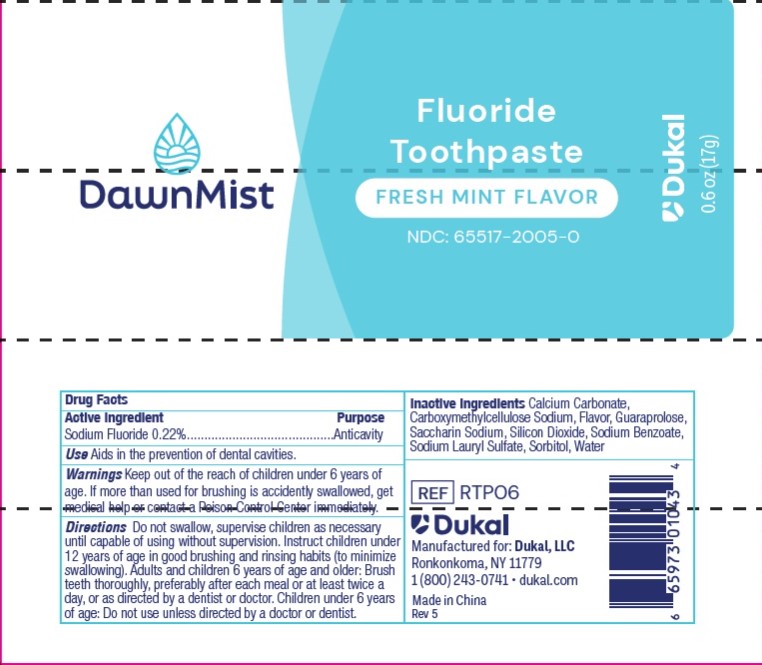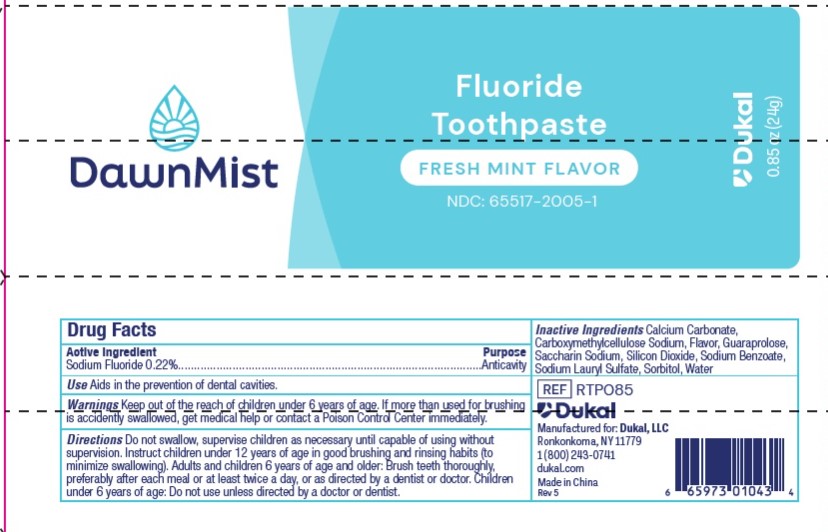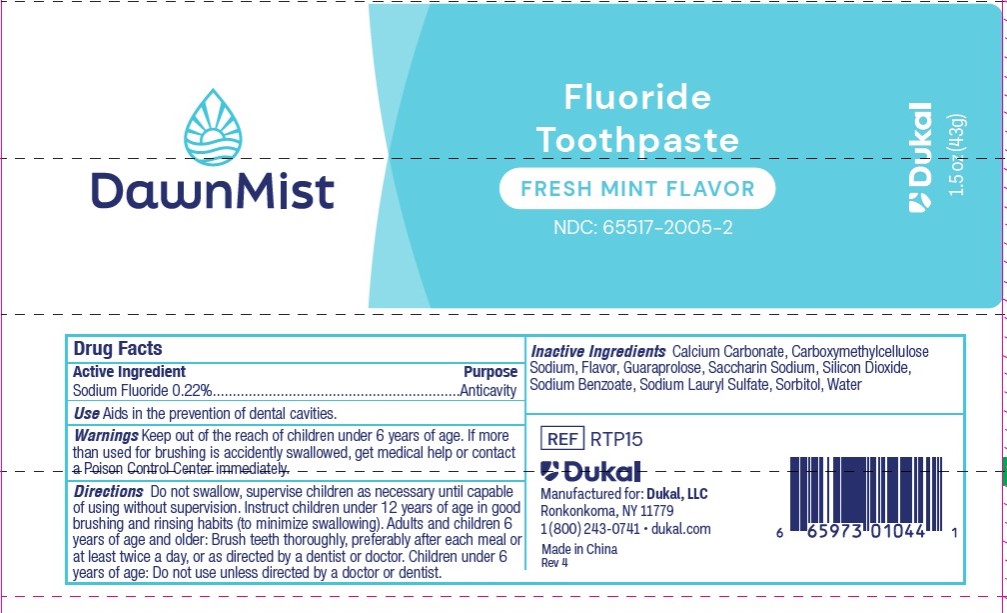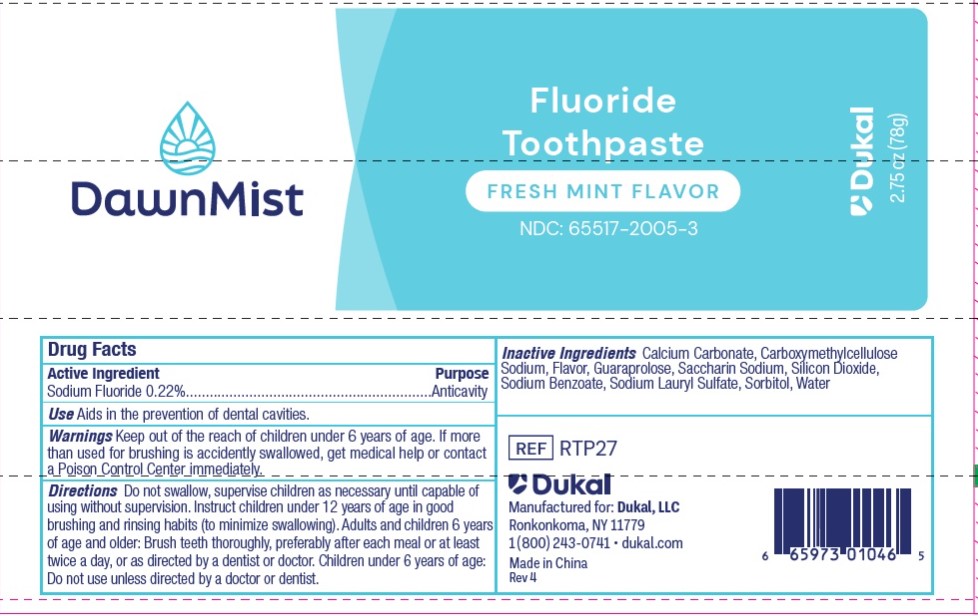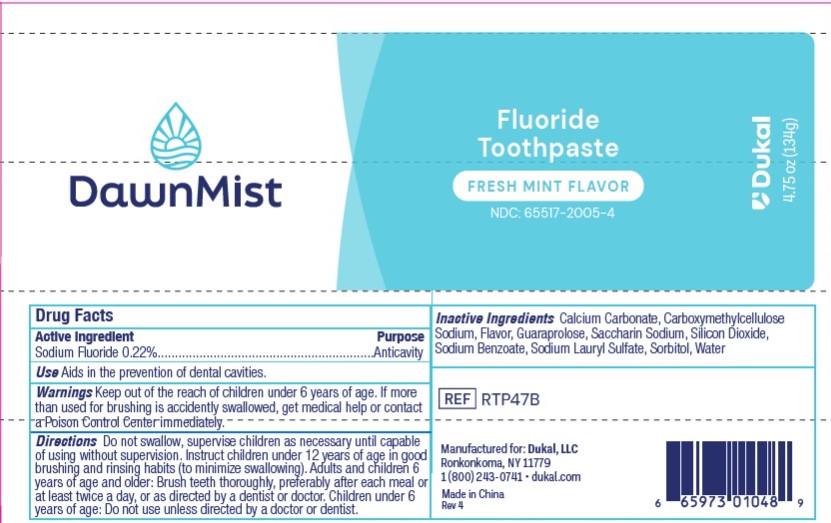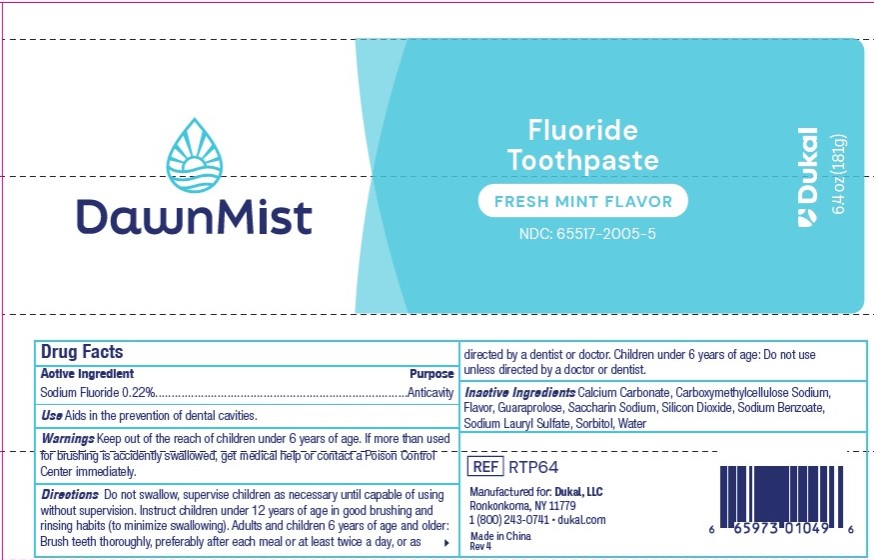 DRUG LABEL: DawnMist
NDC: 65517-2005 | Form: PASTE, DENTIFRICE
Manufacturer: Dukal LLC
Category: otc | Type: HUMAN OTC DRUG LABEL
Date: 20250207

ACTIVE INGREDIENTS: SODIUM FLUORIDE 0.22 g/100 g
INACTIVE INGREDIENTS: SORBITOL; WATER; SACCHARIN SODIUM; CALCIUM CARBONATE; SODIUM BENZOATE; SODIUM LAURYL SULFATE; GUARAPROLOSE (1300 MPA.S AT 1%); SILICON DIOXIDE; CARBOXYMETHYLCELLULOSE SODIUM

65517-2005 - DawnMist Fluoride Toothpaste

DawnMist Fluoride Toothpaste

ACTIVE INGREDIENT

Sodium Fluoride 0.22%

PURPOSE

Anticavity

INDICATIONS AND USAGE

Aids in the prevention of dental cavities.

WARNINGS

KEEP OUT OF REACH OF CHILDREN

Keep out of the reach of children under 6 years of age. If more than used for brushing is accidently swallowed, get medical help or contact a Poison Control Center immediately.

DOSAGE AND ADMINISTRATION

Do not swallow, supervise children as necessary until capable of using without supervision. Instruct Children under 12 years of age in good brushing and rinsing habits (to minimize swallowing). Adults and children 6 years of age and older: Brush teeth thoroughly, preferably after each meal or at least twice a day, or as directed by a dentist or doctor. Children under 6 years of age: Do not use unless directed by a doctor or dentist.

INACTIVE INGREDIENT

Calcium Carbonate, Carboxymethylcellulose Sodium, Flavor, Guaraprolose, Saccharin Sodium, Silicon Dioxide, Sodium Benzoate, Sodium Lauryl Sulfate, Sorbitol, Water

PACKAGE LABEL

DawnMist

Fluoride Toothpaste

FRESH MINT FLAVOR

NDC: 65517-2005-0

Dukal

0.6oz (17g)

PACKAGE LABEL

DawnMist

Fluoride Toothpaste

FRESH MINT FLAVOR

NDC: 65517-2005-1

Dukal

0.85oz (24g)

PACKAGE LABEL

DawnMist

Fluoride Toothpaste

FRESH MINT FLAVOR

NDC: 65517-2005-2

Dukal

1.5oz (43g)

PACKAGE LABEL

DawnMist

Fluoride Toothpaste

FRESH MINT FLAVOR

NDC: 65517-2005-3

Dukal

2.75oz (78g)

PACKAGE LABEL

DawnMist

Fluoride Toothpaste

FRESH MINT FLAVOR

NDC: 65517-2005-4

Dukal

4.75oz (134g)

PACKAGE LABEL

DawnMist

Fluoride Toothpaste

FRESH MINT FLAVOR

NDC: 65517-2005-5

Dukal

6.4oz (181g)